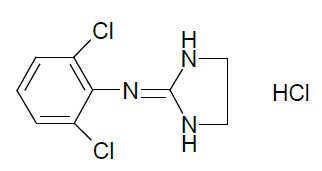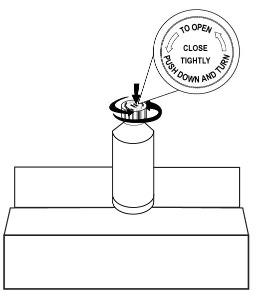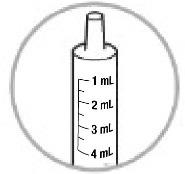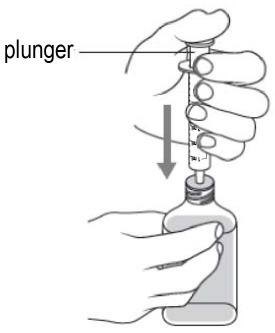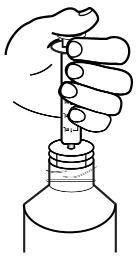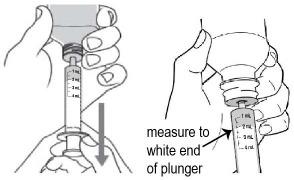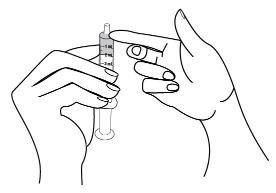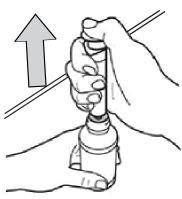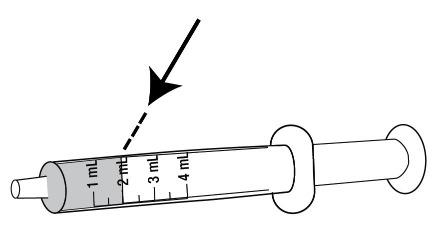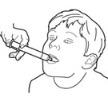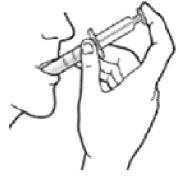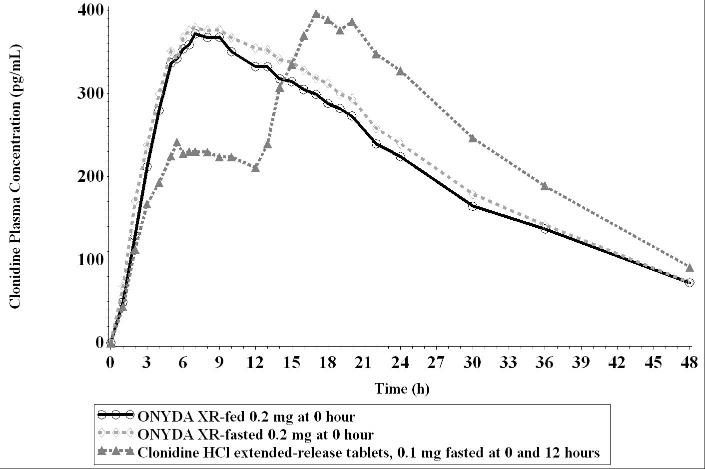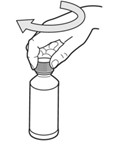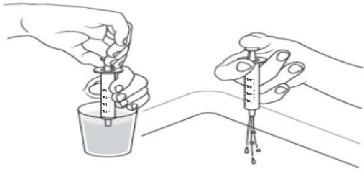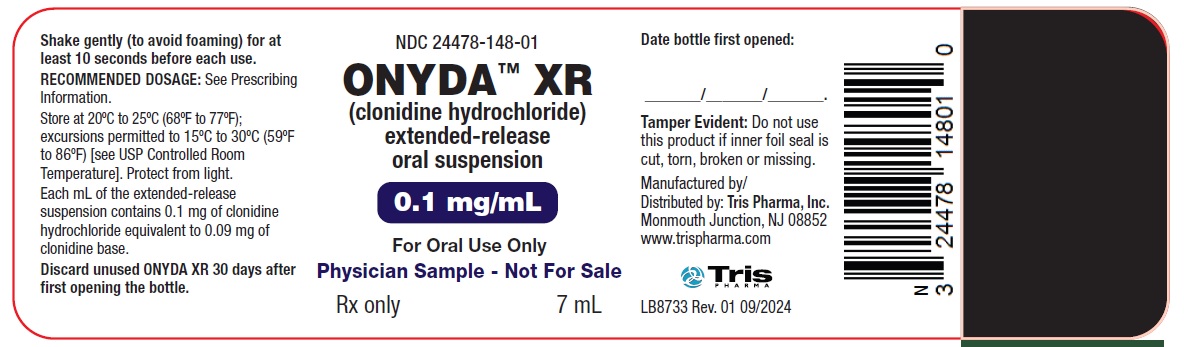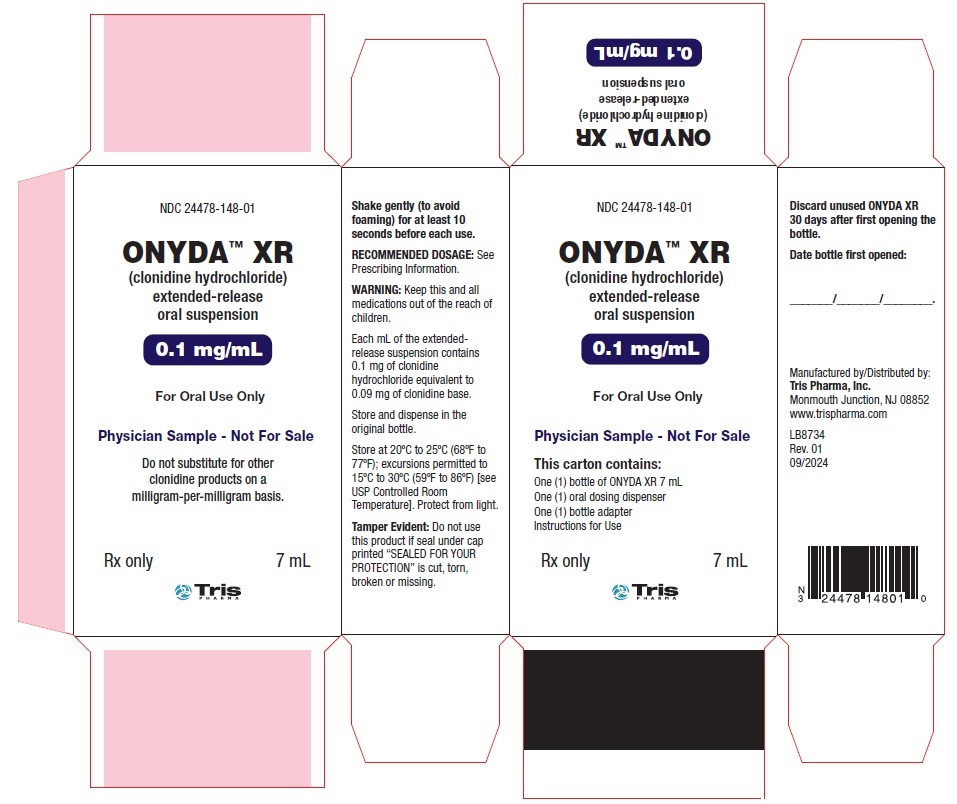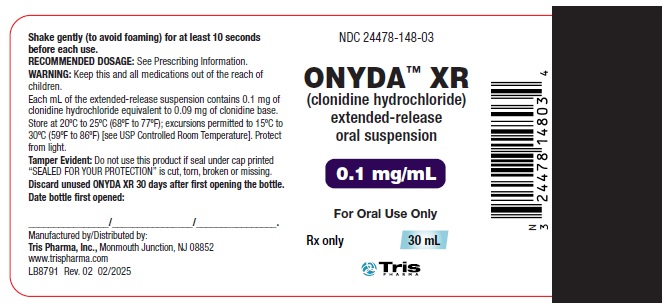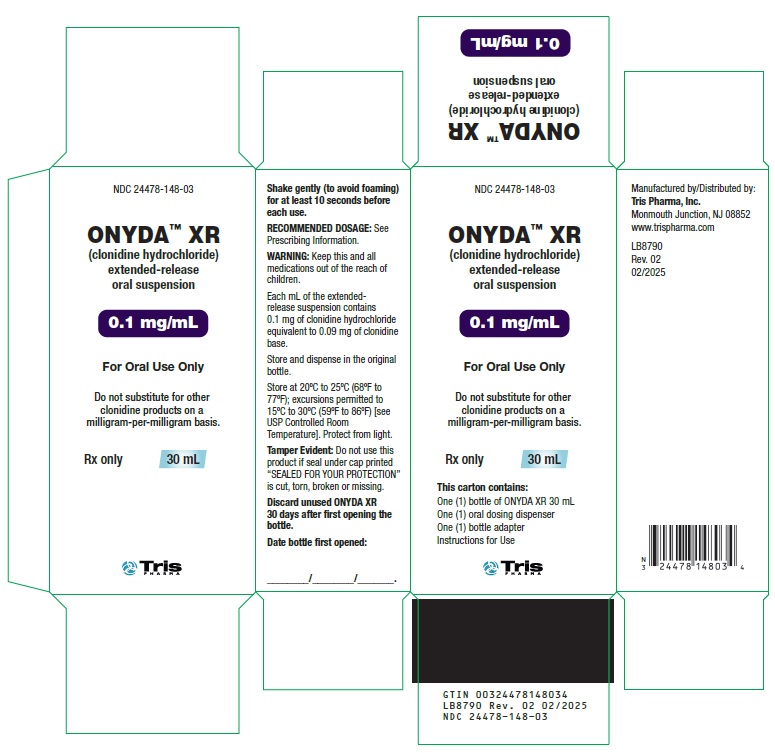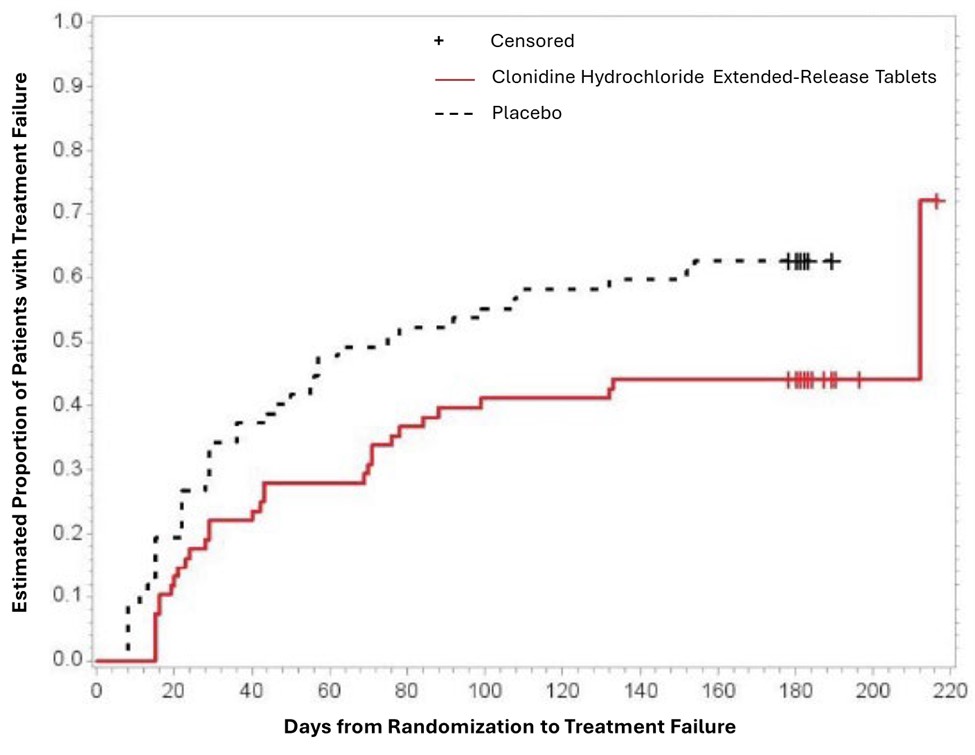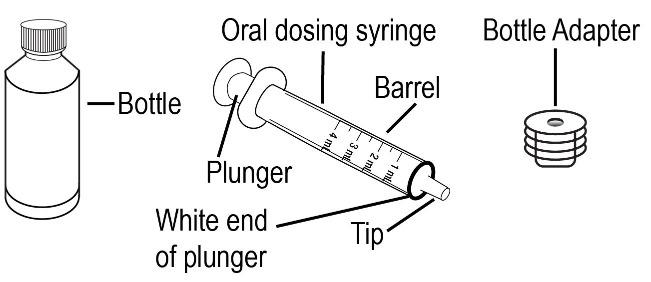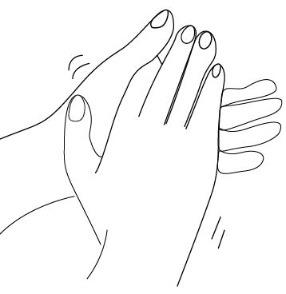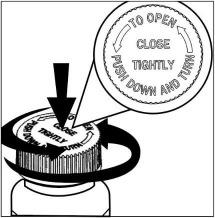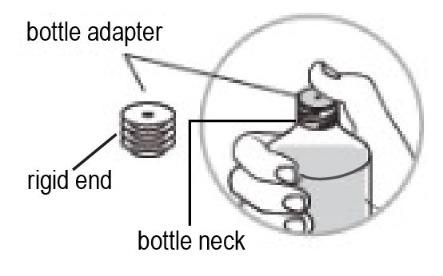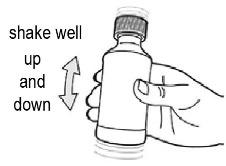 DRUG LABEL: ONYDA XR
NDC: 24478-148 | Form: SUSPENSION, EXTENDED RELEASE
Manufacturer: NextWave Pharmaceuticals, Inc
Category: prescription | Type: HUMAN PRESCRIPTION DRUG LABEL
Date: 20250411

ACTIVE INGREDIENTS: CLONIDINE HYDROCHLORIDE 0.1 mg/1 mL
INACTIVE INGREDIENTS: ANHYDROUS CITRIC ACID; EDETATE DISODIUM; GLYCERIN; METHYLPARABEN; POLYVINYL ACETATE; POVIDONE; POLYSORBATE 80; PROPYLPARABEN; SODIUM POLYSTYRENE SULFONATE; SUCROSE; TRIACETIN; WATER; XANTHAN GUM

HIGHLIGHTS OF PRESCRIBING INFORMATION

These highlights do not include all the information needed to use ONYDATM XR safely and effectively. See full prescribing information for ONYDATM XR.
ONYDATM XR (clonidine hydrochloride) extended-release oral suspension
Initial U.S. Approval: 1974

RECENT MAJOR CHANGES

Warnings and Precautions (5.3) 04/2025

1 INDICATIONS AND USAGE

ONYDA XR is a centrally acting alpha2-adrenergic agonist indicated for the treatment of Attention Deficit Hyperactivity Disorder (ADHD) as monotherapy or as adjunctive therapy to central nervous system (CNS) stimulant medications in pediatric patients 6 years of age and older. (1)

2 DOSAGE AND ADMINISTRATION

- Starting dosage is 0.1 mg of ONYDA XR orally once daily at bedtime with or without food. Dosage may be increased in increments of 0.1 mg per day at weekly intervals. Maximum recommended dosage is 0.4 mg once daily at bedtime. (2.1)
- Do not substitute ONYDA XR for other clonidine products on a mg-per-mg basis because of differing pharmacokinetic profiles. (2.3)
- When discontinuing, taper the dose in decrements of no more than 0.1 mg every 3 to 7 days to avoid rebound hypertension. (2.4)

3 DOSAGE FORMS AND STRENGTHS

Extended-release oral suspension: 0.1 mg clonidine hydrochloride per mL (3)

4 CONTRAINDICATIONS

History of a hypersensitivity reaction to clonidine. Reactions have included generalized rash, urticaria, angioedema. (4)

5 WARNINGS AND PRECAUTIONS

- Hypotension/bradycardia: Titrate slowly and monitor vital signs frequently in patients at risk for hypotension, heart block, bradycardia, syncope, cardiovascular disease, vascular disease, cerebrovascular disease, or chronic renal failure. Measure heart rate and blood pressure prior to initiation of therapy, following dose increases, and periodically while on therapy. Avoid concomitant use of drugs with additive effects unless clinically indicated. Advise patients to avoid becoming dehydrated or overheated. (5.1)
- Somnolence/Sedation: Has been observed with clonidine. Consider the potential for additive sedative effects with CNS depressant drugs. Caution patients against operating heavy equipment or driving until they know how they respond to ONYDA XR (5.2)
- Cardiac Conduction Abnormalities: May worsen sinus node dysfunction and atrioventricular (AV) block, especially in patients taking other sympatholytic drugs. Titrate slowly and monitor vital signs frequently. (5.5)

6 ADVERSE REACTIONS

Most common adverse reactions (incidence at least 5% and twice the rate of placebo) as monotherapy in ADHD: somnolence, fatigue, irritability, nightmare, insomnia, constipation, dry mouth. (6.1)

Most common adverse reactions (incidence at least 5% and twice the rate of placebo) as adjunct therapy to psychostimulant in ADHD: somnolence, fatigue, decreased appetite, dizziness. (6.1)

To report SUSPECTED ADVERSE REACTIONS, contact Tris Pharma, Inc. at (732) 940-0358 or FDA at 1-800-FDA-1088 or www.fda.gov/medwatch.

7 DRUG INTERACTIONS

- CNS Depressants: Clonidine may potentiate the CNS-depressive effects of alcohol, barbiturates or other sedating drugs. (7)
- Tricyclic Antidepressants: May reduce the hypotensive effect of clonidine. (7)
- Drugs Known to Affect Sinus Node Function or AV Nodal Conduction: Avoid use of ONYDA XR with agents known to affect sinus node function or AV nodal conduction (e.g., digitalis, calcium channel blockers and beta-blockers) due to a potential for additive effects such as bradycardia and AV block. (7)
- Antihypertensive drugs: Use caution when coadministered with ONYDA XR. (7)

8 USE IN SPECIFIC POPULATIONS

Renal Impairment: The dosage of ONYDA XR must be adjusted according to the degree of impairment, and patients should be carefully monitored. (8.6, 12.3)

FULL PRESCRIBING INFORMATION

1 INDICATIONS AND USAGE

ONYDA XR is indicated for the treatment of Attention Deficit Hyperactivity Disorder (ADHD) as monotherapy and as adjunctive therapy to central nervous system (CNS) stimulant medications in pediatric patients 6 years of age and older [see Clinical Studies (14)].

2 DOSAGE AND ADMINISTRATION

2.1 Recommended Dosage

The starting dosage of ONYDA XR is 0.1 mg orally once daily at bedtime with or without food [see Clinical Pharmacology (12.3)]. Titrate the dose of ONYDA XR in increments of 0.1 mg per day at weekly intervals depending on clinical response up to the maximum recommended dosage of 0.4 mg once daily at bedtime.

Doses of ONYDA XR higher than 0.4 mg once daily were not evaluated in clinical trials for ADHD and are not recommended.

When ONYDA XR is added to a CNS stimulant, adjust the dose of the CNS stimulant depending on the clinical response to ONYDA XR.

2.2 Administration Instructions

Instruct patients to read the “Instructions for Use” for complete administration instructions.

- Use the oral dosing dispenser and bottle adapter provided with ONYDA XR.
- Ensure that the bottle adapter is firmly inserted into the bottle before first use and keep the adapter in place for the duration of the usage of the bottle.
- Gently shake ONYDA XR with a smooth up and down motion (to avoid foaming) for at least 10 seconds before each administration.
- For the bottles of 30 mL and 60 mL, discard any unused ONYDA XR 30 days after first opening the bottle.
- For the 120 mL bottle, discard any unused ONYDA XR 60 days after first opening the bottle.

2.3 Switching from Other Clonidine Products

For patients switching from another clonidine product, discontinue that treatment, and titrate with ONYDA XR using the titration schedule [see Dosage and Administration (2.1)]. Do not substitute for other clonidine products on a milligram-per-milligram basis because of differing pharmacokinetic profiles [see Clinical Pharmacology (12.3)].

2.4 Discontinuation

When discontinuing ONYDA XR, taper the total daily dose in decrements of no more than 0.1 mg every 3 to 7 days to avoid rebound hypertension [see Warnings and Precautions (5.3)].

2.5 Missed Doses

If a dose of ONYDA XR is missed, skip that dose and take the next dose as scheduled. Do not take more than the prescribed total daily amount of ONYDA XR in any 24-hour period.

3 DOSAGE FORMS AND STRENGTHS

Extended-release oral suspension: Light beige to tan viscous suspension containing 0.1 mg clonidine hydrochloride per mL.

4 CONTRAINDICATIONS

ONYDA XR is contraindicated in patients with a history of a hypersensitivity reaction to clonidine. Reactions have included generalized rash, urticaria, and angioedema [see Warnings and Precautions (5.4) and Adverse Reactions (6)].

5 WARNINGS AND PRECAUTIONS

5.1 Hypotension/Bradycardia

Treatment with ONYDA XR can cause dose-related decreases in blood pressure and heart rate [see Adverse Reactions (6.1)]. Measure heart rate and blood pressure prior to initiation of therapy, following dose increases, and periodically while on therapy. Titrate ONYDA XR slowly in patients with a history of hypotension, and those with underlying conditions that may be worsened by hypotension and bradycardia; e.g., heart block, bradycardia, cardiovascular disease, vascular disease, cerebrovascular disease, or chronic renal failure. In patients who have a history of syncope or may have a condition that predisposes them to syncope, such as hypotension, orthostatic hypotension, bradycardia, or dehydration, advise patients to avoid becoming dehydrated or overheated. Monitor blood pressure and heart rate, and adjust dosages accordingly in patients treated concomitantly with antihypertensives or other drugs that can reduce blood pressure or heart rate or increase the risk of syncope [see Drug Interactions (7)].

5.2 Sedation and Somnolence

Somnolence and sedation were commonly reported adverse reactions in clinical studies with clonidine hydrochloride extended-release tablets. In patients that completed 5 weeks of therapy in a controlled, fixed dose pediatric monotherapy study, 31% of patients treated with 0.4 mg/day and 38% treated with 0.2 mg/day versus 4% of placebo treated patients reported somnolence as an adverse reaction. In patients that completed 5 weeks of therapy in a controlled flexible dose pediatric adjunctive to stimulants study, 19% of patients treated with clonidine hydrochloride extended-release tablets plus a stimulant versus 7% treated with placebo plus a stimulant reported somnolence.

Before using ONYDA XR with other centrally active depressants (such as phenothiazines, barbiturates, or benzodiazepines), consider the potential for additive sedative effects [see Drug Interactions (7)]. Caution patients against operating heavy equipment or driving until they know how they respond to treatment with ONYDA XR. Advise patients to avoid use with alcohol.

5.3 Rebound Hypertension

Abrupt discontinuation of ONYDA XR can cause rebound hypertension. In adults with hypertension, sudden cessation of clonidine extended-release formulation treatment in the 0.2 to 0.6 mg per day range resulted in reports of headache, tachycardia, nausea, flushing, warm feeling, brief lightheadedness, tightness in chest, and anxiety. In adults with hypertension, sudden cessation of treatment with immediate-release clonidine has, in some cases, resulted in symptoms such as nervousness, agitation, headache, and tremor accompanied or followed by a rapid rise in blood pressure and elevated catecholamine concentrations in the plasma. Pediatric patients with gastrointestinal illnesses that lead to vomiting may result in missed doses of ONYDA XR, increasing the risk for rebound hypertension.

No studies evaluating abrupt discontinuation of clonidine hydrochloride extended-release tablets in pediatric patients with ADHD have been conducted; however, to minimize the risk of rebound hypertension, gradually reduce the dose of ONYDA XR in decrements of no more than 0.1 mg every 3 to 7 days. Patients should be instructed not to discontinue ONYDA XR therapy without consulting their physician due to the potential risk of withdrawal effects.

5.4 Allergic Reactions

In patients who have developed localized contact sensitization to clonidine transdermal system, continuation of clonidine transdermal system or use of oral ONYDA XR therapy may be associated with the development of a generalized skin rash.

In patients who develop an allergic reaction from clonidine transdermal system, use of ONYDA XR may also elicit an allergic reaction (including generalized rash, urticaria, or angioedema).

5.5 Cardiac Conduction Abnormalities

The sympatholytic action of clonidine may worsen sinus node dysfunction and atrioventricular (AV) block, especially in patients taking other sympatholytic drugs. There have been post-marketing reports of patients with conduction abnormalities and/or taking other sympatholytic drugs who developed severe bradycardia requiring intravenous (IV) atropine, IV isoproterenol, and temporary cardiac pacing while taking clonidine. Titrate ONYDA XR slowly and monitor vital signs frequently in patients with cardiac conduction abnormalities or patients concomitantly treated with other sympatholytic drugs.

6 ADVERSE REACTIONS

The following serious adverse reactions are described in greater detail elsewhere in labeling:

- Hypotension/bradycardia [see Warnings and Precautions (5.1)]
- Sedation and somnolence [see Warnings and Precautions (5.2)]
- Rebound hypertension [see Warnings and Precautions (5.3)]
- Allergic reactions [see Warnings and Precautions (5.4)]
- Cardiac Conduction Abnormalities [see Warnings and Precautions (5.5)]

6.1 Clinical Trial Experience

Because clinical trials are conducted under widely varying conditions, adverse reaction rates observed in the clinical trials of a drug cannot be directly compared to rates in the clinical trials of another drug and may not reflect the rates observed in practice.

The safety of ONYDA XR for the treatment of ADHD in pediatric patients 6 years and older is based upon adequate and well-controlled studies of clonidine hydrochloride extended-release tablets (referred to as “clonidine hydrochloride extended-release” in this section). The safety results of these adequate and well-controlled studies of clonidine hydrochloride extended-release tablets are presented below.

Two clonidine hydrochloride extended-release ADHD clinical studies (Study 1 and Study 2) evaluated 256 patients in two 8-week placebo-controlled studies.

A third clonidine hydrochloride extended-release ADHD clinical study (Study 3) evaluated 135 pediatric patients 6 to 17 years of age in a 40-week placebo-controlled randomized‑withdrawal study.

Study 1: Fixed-dose clonidine hydrochloride extended-release Monotherapy

Study 1 was a short-term, multi-center, randomized, double-blind, placebo-controlled study of two fixed doses (0.2 mg/day or 0.4 mg/day) of clonidine hydrochloride extended-release in pediatric patients 6 to 17 years of age who met DSM-IV criteria for ADHD hyperactive or combined inattentive/hyperactive subtypes.

Most Common Adverse Reactions (incidence of ≥ 5% and at least twice the rate of placebo): somnolence, fatigue, irritability, insomnia, nightmare, constipation, dry mouth.

Adverse Reactions Leading to Discontinuation of clonidine hydrochloride extended-release: Five patients (7%) in the low dose group (0.2 mg), 15 patients (20%) in the high dose group (0.4 mg), and 1 patient in the placebo group (1%) reported adverse reactions that led to discontinuation. The most common adverse reactions that led to discontinuation were somnolence and fatigue.

Commonly observed adverse reactions (incidence of ≥2% in either active treatment group and greater than the rate on placebo) during the treatment period are listed in Table 1.

Table 1: Common Adverse Reactions Occurring in ≥2%of Patients Treated with Clonidine Hydrochloride Extended-Release Tablets and Greater than the Rate of Placebo in the Fixed-Dose Monotherapy Trial -Treatment Period (Study 1)

Preferred Term | Clonidine hydrochloride extended-release tablets; 0.2 mg/day; N=76; (%) | Clonidine hydrochloride extended-release tablets; 0.4 mg/day; N=78; (%) | Placebo N=76; (%)
PSYCHIATRIC DISORDERS; Somnolence*; Nightmare; Emotional Disorder; Aggression; Tearfulness; Enuresis; Sleep Terror; Poor Quality Sleep | 38; 4; 4; 3; 1; 0; 3; 0 | 31; 9; 4; 1; 3; 4; 0; 3 | 4; 0; 1; 0; 0; 0; 0; 1
NERVOUS SYSTEM DISORDERS; Headache; Insomnia; Tremor; Abnormal Sleep-Related Event | 20; 5; 1; 3 | 13; 6; 4; 1 | 16; 1; 0; 0
GASTRO-INTESTINAL DISORDERS; Upper Abdominal Pain; Nausea; Constipation; Dry Mouth | 15; 4; 1; 0 | 10; 5; 6; 5 | 12; 3; 0; 1
GENERAL DISORDERS; Fatigue†; Irritability | 16; 9 | 13; 5 | 1; 4
CARDIAC DISORDERS; Dizziness; Bradycardia | 7; 0 | 3; 4 | 5; 0
INVESTIGATIONS; Increased Heart Rate | 0 | 3 | 0
METABOLISM AND NUTRITION DISORDERS; Decreased Appetite | 3 | 4 | 4

* Somnolence includes the terms "somnolence" and "sedation".

† Fatigue includes the terms "fatigue" and "lethargy".

Commonly observed adverse reactions (incidence of ≥2% in either active treatment group and greater than the rate on placebo) during the taper period are listed in Table 2.

Table 2: Common Adverse Reactions Occurring in ≥2% of Patients Treated with Clonidine Hydrochloride Extended-Release Tablets and Greater than the Rate of Placebo in the Fixed-Dose Monotherapy Trial -Taper Period* (Study 1)

Preferred Term | Clonidine hydrochloride extended-release tablets; 0.2 mg/day; N=76; (%) | Clonidine hydrochloride extended-release tablets; 0.4 mg/day; N=78; (%) | Placebo; N=76; (%)
Abdominal Pain Upper | 0 | 6 | 3
Headache | 5 | 2 | 3
Gastrointestinal Viral | 0 | 5 | 0
Somnolence | 2 | 3 | 0
Heart Rate Increased | 0 | 3 | 0
Otitis Media Acute | 3 | 0 | 0

* Taper Period: 0.2 mg dose, week 8; 0.4 mg dose, weeks 6-8; Placebo dose, weeks 6-8

Study 2: Flexible-dose clonidine hydrochloride extended-release as Adjunctive Therapy to Psychostimulants

Study 2 was a short-term, randomized, double-blind, placebo-controlled study of a flexible dose of clonidine hydrochloride extended-release as adjunctive therapy to a psychostimulant in pediatric patients 6 to 17 years of age who met DSM-IV criteria for ADHD hyperactive or combined inattentive/hyperactive subtypes, during which clonidine hydrochloride extended‑release was initiated at 0.1 mg/day and titrated up to 0.4 mg/day over a 3-week period. Most clonidine hydrochloride extended-release treated patients (75.5%) were escalated to the maximum dose of 0.4 mg/day.

Most Common Adverse Reactions (incidence of ≥ 5% and at least twice the rate of placebo): somnolence, fatigue, decreased appetite, dizziness.

Adverse Reactions Leading to Discontinuation: There was one patient in the clonidine hydrochloride extended-release + stimulant (group (1%) who discontinued because of an adverse event (severe bradyphrenia, with severe fatigue).

Commonly observed adverse reactions (incidence of ≥2% in the treatment group and greater than the rate on placebo) during the treatment period are listed in Table 3.

Table 3: Common Adverse Reactions Occurring in ≥2% of Patients Treated with Clonidine Hydrochloride Extended-Release Tablets and Greater than the Rate of Placebo in the Flexible-Dose Adjunctive to Stimulant Therapy Trial -Treatment Period (Study 2)

Preferred Term | Clonidine hydrochloride extended-release tablets + Stimulant; N=102; (%) | PBO+Stimulant; N=96; (%)
PSYCHIATRIC DISORDERS; Somnolence+; Aggression; Affect Lability; Emotional Disorder | 19; 2; 2; 2 | 7; 1; 1; 0
GENERAL DISORDERS; Fatigue†; Irritability | 14; 2 | 4; 7
NERVOUS SYSTEM DISORDERS; Headache; Insomnia | 7; 4 | 12; 3
GASTRO-INTESTINAL DISORDERS; Upper Abdominal Pain | 7 | 4
RESPIRATORY DISORDERS; Nasal Congestion | 2 | 2
METABOLISM AND NUTRITION DISORDERS; Decreased Appetite | 6 | 3
CARDIAC DISORDERS; Dizziness | 5 | 1

^+Somnolence includes the terms: "somnolence" and "sedation"

† Fatigue includes the terms "fatigue" and "lethargy"

Commonly observed adverse reactions (incidence of ≥2% in the treatment group and greater than the rate on placebo) during the taper period are listed in Table 4.

Table 4: Common Adverse Reactions Occurring in ≥2% of Patients Treated with Clonidine Hydrochloride Extended-Release Tablets and Greater than the Rate of Placebo in the Flexible-Dose Adjunctive to Stimulant Therapy Trial -Taper Period^+ (Study 2)

Preferred Term | Clonidine hydrochloride extended-release tablets + Stimulant; N=102; (%) | Placebo+Stimulant; N=96; (%)
Nasal Congestion | 4 | 2
Headache | 3 | 1
Irritability | 3 | 2
Throat Pain | 3 | 1
Gastroenteritis Viral | 2 | 0
Rash | 2 | 0

^+Taper Period: weeks 6-8

Adverse Reactions Leading to Discontinuation

Thirteen percent (13%) of patients receiving clonidine hydrochloride extended-release discontinued from the pediatric monotherapy study due to adverse reactions, compared to 1% in the placebo group. The most common adverse reactions leading to discontinuation of clonidine hydrochloride extended-release monotherapy treated patients were somnolence/sedation (5%) and fatigue (4%).

Effect on Blood Pressure and Heart Rate

In patients that completed 5 weeks of treatment in a controlled, fixed-dose monotherapy study in pediatric patients, during the treatment period the maximum placebo-subtracted mean change in systolic blood pressure was -4.0 mmHg on clonidine hydrochloride extended-release 0.2 mg/day and -8.8 mmHg on clonidine hydrochloride extended-release 0.4 mg/day. The maximum placebo-subtracted mean change in diastolic blood pressure was -4.0 mmHg on clonidine hydrochloride extended-release 0.2 mg/day and -7.3 mmHg on clonidine hydrochloride extended-release 0.4 mg/day. The maximum placebo-subtracted mean change in heart rate was ‑4.0 beats per minute on clonidine hydrochloride extended-release 0.2 mg/day and -7.7 beats per minute on clonidine hydrochloride extended-release 0.4 mg/day.

During the taper period of the fixed-dose monotherapy study the maximum placebo-subtracted mean change in systolic blood pressure was +3.4 mmHg on clonidine hydrochloride extended‑release 0.2 mg/day and -5.6 mmHg on clonidine hydrochloride extended-release 0.4 mg/day. The maximum placebo-subtracted mean change in diastolic blood pressure was +3.3 mmHg on clonidine hydrochloride extended-release 0.2 mg/day and -5.4 mmHg on clonidine hydrochloride extended-release 0.4 mg/day. The maximum placebo-subtracted mean change in heart rate was -0.6 beats per minute on clonidine hydrochloride extended-release 0.2 mg/day and -3.0 beats per minute on clonidine hydrochloride extended-release 0.4 mg/day.

6.2 Postmarketing Experience

The following adverse reactions have been identified during post-approval use of clonidine hydrochloride extended-release tablets (and excludes those already mentioned in Section 6.1). Because these reactions are reported voluntarily from a population of uncertain size, it is not always possible to reliably estimate their frequency or establish a causal relationship to drug exposure.

Psychiatric: hallucinations

Cardiovascular: Q-T prolongation

7 DRUG INTERACTIONS

The interactions of ONYDA XR with co-administration of other drugs have not been studied. The drug interaction data provided in this section is based on oral immediate-release clonidine formulations.

Table 5 displays clinically important drug interactions with ONYDA XR.

Table 5: Clinically Important Drug Interactions with ONYDA XR

Antihypertensive drugs
Clinical Implication | Concomitant use of antihypertensive drugs with clonidine potentiates the hypotensive effects of clonidine.
Intervention | Monitor blood pressure and heart rate, and adjust dosage of ONYDA XR accordingly in patients treated concomitantly with antihypertensives [see Warnings and Precautions (5.1)].
CNS depressants
Clinical Implication | Concomitant use of CNS depressants with clonidine potentiates the sedating effects [see Warnings and Precautions (5.2)].
Intervention | Avoid concomitant use of CNS depressants with ONYDA XR.
Drugs that affect sinus node function or AV node conduction (e.g., digitalis, calcium channel blockers, beta blockers)
Clinical Implication | Concomitant use of drugs that affect sinus node function or AV node conduction with clonidine potentiate bradycardia and risk of AV block [see Warnings and Precautions (5.5)].
Intervention | Avoid concomitant use of drugs that affect sinus node function or AV node conduction with ONYDA XR.
Tricyclic antidepressants
Clinical Implication | Concomitant use of tricyclic antidepressants with clonidine can increase blood pressure and may counteract the hypotensive effects of clonidine.
Intervention | Monitor blood pressure and adjust dosage of ONYDA XR as needed.

8 USE IN SPECIFIC POPULATIONS

8.1 Pregnancy

Pregnancy Exposure Registry

There is a pregnancy exposure registry that monitors pregnancy outcomes in women exposed to ADHD medications, including ONYDA XR, during pregnancy. Healthcare providers are encouraged to advise patients to register by calling the National Pregnancy Registry for Psychiatric Medications at 1-866-961-2388 or visiting online at https://womensmentalhealth.org/adhd-medications/.

Risk Summary

Prolonged experience with clonidine in pregnant women over several decades, based on published literature, including controlled trials, a retrospective cohort study and case reports, have not identified a drug associated risk of major birth defects, miscarriage, and adverse maternal or fetal outcomes. In animal embryofetal studies, increased resorptions were seen in rats and mice administered oral clonidine hydrochloride from implantation through organogenesis at 10 and 5 times, respectively, the maximum recommended human dose (MRHD) given to adolescents on a mg/m^2 basis. No developmental effects were seen in rabbits administered oral clonidine hydrochloride during organogenesis at doses up to 3 times the MRHD (see Data).

The estimated background risk of major birth defects and miscarriage for the indicated population is unknown. All pregnancies have a background risk of birth defect, loss, or other adverse outcomes. In the U.S. general population, the estimated background risk of major birth defects and miscarriages in clinically recognized pregnancies is 2 to 4% and 15 to 20%, respectively.

Data

Animal Data

Oral administration of clonidine hydrochloride to pregnant rabbits during the period of embryo/fetal organogenesis at doses of up to 80 mcg/kg/day (approximately 3 times the oral maximum recommended daily dose [MRHD] of 0.4 mg/day given to adolescents on a mg/m^2 basis) produced no developmental effects. In pregnant rats, however, doses as low as 15 mcg/kg/day (1/3 the MRHD given to adolescents on a mg/m^2 basis) were associated with increased resorptions in a study in which dams were treated continuously from 2 months prior to mating and throughout gestation. Increased resorptions were not associated with treatment at the same or at higher dose levels (up to 3 times the MRHD) when treatment of the dams was restricted to gestation days 6-15. Increases in resorptions were observed in both rats and mice at 500 mcg/kg/day (10 and 5 times the MRHD in rats and mice, respectively) or higher when the animals were treated on gestation days 1-14; 500 mcg/kg/day was the lowest dose employed in this study.

8.2 Lactation

Risk Summary

Based on published lactation studies, clonidine hydrochloride is present in human milk at relative infant doses ranging from 4.1% to 8.4% of the maternal weight-adjusted dosage. Although in most cases, there were no reported adverse effects in breastfed infants exposed to clonidine, there is one case report of sedation, hypotonia, and apnea in an infant exposed to clonidine through breast milk. If an infant is exposed to clonidine through breastmilk, monitor for symptoms of hypotension and bradycardia, such as sedation, lethargy, tachypnea and poor feeding (see Clinical Considerations). The developmental and health benefits of breastfeeding should be considered along with the mother’s clinical need for ONYDA XR and any potential adverse effects on the breastfed child from ONYDA XR or from the underlying maternal condition. Exercise caution when ONYDA XR is administered to a nursing woman.

Clinical Considerations

Monitor breastfeeding infants exposed to ONYDA XR through breast milk for symptoms of hypotension and/or bradycardia such as sedation, lethargy, tachypnea, and poor feeding.

8.3 Females and Males of Reproductive Potential

Infertility

Findings in animal studies revealed that ONYDA XR may impair fertility in females and males of reproductive potential [see Nonclinical Toxicology (13.1)].

8.4 Pediatric Use

The safety and efficacy of clonidine hydrochloride extended-release in the treatment of ADHD have been established in pediatric patients 6 to 17 years of age. Use of clonidine hydrochloride extended-release in pediatric patients 6 to 17 years of age is supported by three adequate and well-controlled studies; a short-term, placebo-controlled monotherapy trial, a short-term adjunctive therapy trial and a longer-term randomized monotherapy trial [see Clinical Studies (14)]. Safety and efficacy in pediatric patients below the age of 6 years has not been established.

Juvenile Animal Data

In studies in juvenile rats, clonidine hydrochloride alone or in combination with methylphenidate had an effect on bone growth at clinically relevant doses and produced a slight delay in sexual maturation in males at 3 times the maximum recommended human dose (MRHD) for clonidine and methylphenidate.

In a study where juvenile rats were treated orally with clonidine hydrochloride from day 21 of age to adulthood, a slight delay in onset of preputial separation (delayed sexual maturation) was seen in males treated with 300 mcg/kg/day, which is approximately 3 times the MRHD of 0.4 mg/day on a mg/m^2 basis. The no-effect dose was 100 mcg/kg/day, which is approximately equal to the MRHD. There was no drug effects on fertility or on other measures of sexual or neurobehavioral development.

In a study where juvenile rats were treated with clonidine alone (300 mcg/kg/day) or in combination with methylphenidate (10 mg/kg/day in females and 50/30 mg/kg/day in males; the dose was lowered from 50 to 30 mg/kg/day in males due to self-injurious behavior during the first week of treatment) from day 21 of age to adulthood, decreases in bone mineral density and mineral content were observed in males treated with 300 mcg/kg/day clonidine alone and in combination with 50/30 mg/kg/day methylphenidate and a decrease in femur length was observed in males treated with the combination at the end of the treatment period. These doses are approximately 3 times the MRHD of 0.4 mg/day clonidine and 54 mg/day methylphenidate on a mg/m^2 basis. All these effects in male were not reversed at the end of a 4-week recovery period. In addition, similar findings were seen in males treated with a lower dose of clonidine (30 mcg/kg/day) in combination with 50 mg/kg/day of methylphenidate and a decrease in femur length was observed in females treated with clonidine alone at the end of the recovery period. These effects were accompanied by a decrease in body weight gain in treated animals during the treatment period but the effect was reversed at the end of the recovery period. A delay in preputial separation (sexual maturation) was observed in males treated with the combination treatment of 300 mcg/kg/day clonidine and 50/30 mg/kg/day methylphenidate. There was no effect on reproduction or sperm analysis in these males.

8.6 Renal Impairment

The impact of renal impairment on the pharmacokinetics of clonidine in pediatric patients has not been assessed. The initial dosage of ONYDA XR should be based on degree of impairment. Monitor patients carefully for hypotension and bradycardia, and titrate to higher doses cautiously. Since only a minimal amount of clonidine is removed during routine hemodialysis, there is no need to give supplemental ONYDA XR following dialysis.

10 OVERDOSAGE

Hypertension may develop early and may be followed by hypotension, bradycardia, respiratory depression, hypothermia, drowsiness, decreased or absent reflexes, weakness, irritability and miosis. The frequency of CNS depression may be higher in pediatric patients than adults. Large overdoses may result in reversible cardiac conduction defects or dysrhythmias, apnea, coma and seizures. Signs and symptoms of overdose generally occur within 30 minutes to two hours after exposure.

Consider contacting the Poison Help line (1-800-222-1222) or a medical toxicologist for additional overdose management recommendations.

11 DESCRIPTION

ONYDA XR contains clonidine hydrochloride, a centrally acting alpha2-adrenergic agonist. Clonidine hydrochloride is an imidazoline derivative and exists as a mesomeric compound. The chemical name is 2-[(2,6-dichlorophenyl)imino]imidazolidine hydrochloride. The following is the structural formula:

The molecular formula of clonidine hydrochloride is C9H9Cl2N3•HCl and the molecular weight is 266.5. The pKa is 8.05.

Clonidine hydrochloride is an odorless, bitter, white to almost white, crystalline powder soluble in water and alcohol. The pH of a 5% solution in water is between 3.5 and 5.5.

ONYDA XR is an extended-release suspension for oral administration. Each mL of ONYDA XR contains 0.09 mg clonidine equivalent to 0.1 mg clonidine hydrochloride (0.095 mg clonidine hydrochloride complexed with sodium polystyrene sulfonate and 0.005 mg clonidine hydrochloride). The pH of ONYDA XR is between 2.8 and 4.

The inactive ingredients are anhydrous citric acid, edetate disodium, glycerin, modified starch, methylparaben, orange flavor, polyvinyl acetate dispersion 30%, povidone, polysorbate 80, propylparaben, purified water, sucrose, sodium polystyrene sulfonate, triacetin, xanthan gum.

12 CLINICAL PHARMACOLOGY

12.1 Mechanism of Action

Clonidine stimulates alpha2-adrenergic receptors in the brain. Clonidine is not a central nervous system stimulant. The mechanism of action of clonidine in ADHD is not known.

12.2 Pharmacodynamics

Clonidine is a known antihypertensive agent. By stimulating alpha2-adrenergic receptors in the brain stem, clonidine reduces sympathetic outflow from the central nervous system and decreases peripheral resistance, renal vascular resistance, heart rate, and blood pressure.

12.3 Pharmacokinetics

Immediate-release clonidine hydrochloride, extended-release clonidine hydrochloride tablets, and ONYDA XR have different pharmacokinetic characteristics. Dose substitution on a milligram for milligram basis will result in differences in exposures [see Dosage and Administration (2.3)].

Absorption

Following a single 0.2 mg dose of ONYDA XR in 20 healthy adult subjects under fasting conditions in a crossover study, the median (range) time to peak plasma concentrations (Tmax) for clonidine was 7.50 (4 –17) hours after dosing. Peak concentration (Cmax) was 95.6% of the Cmax of clonidine extended-release tablet 0.1 mg administered at 0 and 12 hours under fasting conditions. The relative bioavailability of ONYDA XR compared with an equal dose of clonidine extended-release tablet was 96.1%.

After oral administration of 0.2 mg of ONYDA XR once daily over 5 days under fasted conditions in healthy adult subjects, the peak steady state plasma concentration (Cmax.ss) was 107.9%, and steady state relative bioavailability (AUCt, ss) was 97.7% compared with 0.1 mg of clonidine extended-release tablet administered twice daily under fasting conditions. The minimum concentration at steady state (Cmin,ss) of ONYDA XR was about 26% lower than that of the equal dose of clonidine extended-release tablet.

Following oral administration of an immediate release formulation in healthy adult subjects, plasma clonidine concentration peaks in approximately 3 to 5 hours.

A comparison across studies suggests that the Cmax is 50% lower for clonidine hydrochloride extended-release tablets compared to immediate-release clonidine hydrochloride.

Effect of Food

Food had no effect on plasma exposures of clonidine after administration of ONYDA XR (see Figure 1).

Figure 1: Mean Clonidine Concentration-Time Profiles After Single Dose Administration

Elimination

The plasma half-life of immediate-release clonidine ranges from 12 to 16 hours. The half-life increases up to 41 hours in patients with severe impairment of renal function.

Metabolism

About 50% of the absorbed dose is metabolized in the liver.

Excretion

Following oral administration about 40% to 60% of the absorbed dose is recovered in the urine as unchanged drug in 24 hours. Although studies of the effect of renal impairment and studies of clonidine excretion have not been performed with ONYDA XR, results are expected to be similar to those of the immediate-release formulation.

Specific Populations

Pediatric patients

Plasma clonidine concentrations in pediatric patients 6 to 17 years (0.1 mg twice daily and 0.2 mg twice daily of clonidine hydrochloride extended-release tablets) with ADHD are greater than those of adults with hypertension, with pediatric patients 6 to 17 years receiving higher doses on a mg/kg basis. Body weight normalized clearance (CL/F) in pediatric patients aged 6 to 17 years was higher than CL/F observed in adults with hypertension. Clonidine concentrations in plasma increased with increases in dose over the dose range of 0.2 to 0.4 mg/day. Clonidine CL/F was independent of dose administered over the 0.2 to 0.4 mg/day dose range. Clonidine CL/F appeared to decrease slightly with increases in age over the range of 6 to 17 years, and females had a 23% lower CL/F than males. The incidence of "sedation-like" events (somnolence and fatigue) appeared to be independent of clonidine dose or concentration within the studied dose range in the titration study. Results from the add-on study showed that clonidine CL/F was 11% higher in patients who were receiving methylphenidate and 44% lower in those receiving amphetamine compared to subjects not on adjunctive therapy.

Drug Interaction Studies

Alcohol: In an in vitro alcohol-induced dose dumping study, a significantly faster and more variable ONYDA XR drug release was observed in the presence of 20% alcohol, but not with 5% or 10% alcohol, when compared to 0% alcohol.

13 NONCLINICAL TOXICOLOGY

13.1 Carcinogenesis, Mutagenesis and Impairment of Fertility

Carcinogenesis

Clonidine hydrochloride was not carcinogenic when administered in the diet of rats (for up to 132 weeks) or mice (for up to 78 weeks) at doses of up to 1,620 (male rats), 2,040 (female rats), or 2,500 (mice) mcg/kg/day. These doses are approximately 20, 25, and 15 times, respectively, the maximum recommended human dose (MRHD) of 0.4 mg/day on a mg/m^2 basis.

Mutagenesis

There was no evidence of genotoxicity in the Ames test for mutagenicity or mouse micronucleus test for clastogenicity.

Impairment of Fertility

In a reproduction study fertility of female rats appeared to be adversely affected at dose levels of 500 and 2,000 mcg/kg/day (10 and 40 times the MRHD on a mg/m^2 basis). Lower doses have not been adequately evaluated and a no adverse effect level could not be established.

14 CLINICAL STUDIES

The efficacy of ONYDA XR for the treatment of ADHD in pediatric patients 6 years of age and older is based upon adequate and well-controlled studies of clonidine hydrochloride extended-release tablets (referred to as “clonidine hydrochloride extended-release” in this section). The efficacy results of these adequate and well-controlled studies of clonidine hydrochloride extended-release tablets are presented below.

Efficacy of clonidine hydrochloride extended-release in the treatment of ADHD was established in pediatric patients 6 to 17 years in:

- One short-term, placebo-controlled monotherapy trial (Study 1)
- One short-term adjunctive therapy to psychostimulants trial (Study 2)
- One randomized withdrawal trial as monotherapy (Study 3)

Short-term Monotherapy and Adjunctive Therapy to Psychostimulant Studies for ADHD

The efficacy of clonidine hydrochloride extended-release in the treatment of ADHD was established in 2 (one monotherapy and one adjunctive therapy) placebo-controlled trials in pediatric patients aged 6 to 17 years, who met DSM-IV criteria of ADHD hyperactive or combined hyperactive/inattentive subtypes. Signs and symptoms of ADHD were evaluated using the investigator administered and scored ADHD Rating Scale-IV-Parent Version (ADHDRS-IV) total score including hyperactive/impulsivity and inattentive subscales. Study 1 was an 8-week randomized, double-blind, placebo-controlled, fixed dose study of pediatric patients 6 to 17 years (N=236) with a 5-week primary efficacy endpoint. Patients were randomly assigned to one of the following three treatment groups: clonidine hydrochloride extended-release 0.2 mg/day (N=78), clonidine hydrochloride extended-release 0.4 mg/day (N=80), or placebo (N=78). Dosing for the clonidine hydrochloride extended-release groups started at 0.1 mg/day and was titrated in increments of 0.1 mg/week to their respective dose (as divided doses). Patients were maintained at their dose for a minimum of 2 weeks before being gradually tapered down to 0.1 mg/day at the last week of treatment. At both doses, improvements in ADHD symptoms were statistically significantly superior in clonidine hydrochloride extended-release-treated patients compared with placebo-treated patients at the end of 5 weeks as measured by the ADHDRS-IV total score (Table 6). Study 2 was an 8-week randomized, double-blind, placebo-controlled, flexible dose study in pediatric patients 6 to 17 years (N=198) with a 5-week primary efficacy end point. Patients had been treated with a psychostimulant (methylphenidate or amphetamine) for four weeks with inadequate response. Patients were randomly assigned to one of two treatment groups: clonidine hydrochloride extended-release adjunct to a psychostimulant (N=102) or psychostimulant alone (N=96). The clonidine hydrochloride extended-release dose was initiated at 0.1 mg/day and doses were titrated in increments of 0.1 mg/week up to 0.4 mg/day, as divided doses, over a 3-week period based on tolerability and clinical response. The dose was maintained for a minimum of 2 weeks before being gradually tapered to 0.1 mg/day at the last week of treatment. ADHD symptoms were statistically significantly improved in clonidine hydrochloride extended-release plus stimulant group compared with the stimulant alone group at the end of 5 weeks as measured by the ADHDRS-IV total score (Table 6).

Table 6: Short-Term Trials

Study Number | Treatment Group | Primary Efficacy Measure: ADHDRS-IV Total Score
Study Number | Treatment Group | Mean Baseline Score (SD) | LS Mean Change from Baseline (SE) | Placebo-subtracted Differencea (95% CI)
Study 1 | Clonidine hydrochloride extended-release tablets; (0.2 mg/day) | 43.8 (7.47) | -15.0 (1.38) | -8.5 (-12.2, -4.8)
Study 1 | Clonidine hydrochloride extended-release tablets (0.4 mg/day) | 44.6 (7.73) | -15.6 (1.33) | -9.1 (-12.8, -5.5)
Study 1 | Placebo | 45.0 (8.53) | -6.5 (1.35) | ----------
Study 2 | Clonidine hydrochloride extended-release tablets (0.4 mg/day) + Psychostimulant | 38.9 (6.95) | -15.8 (1.18) | -4.5 (-7.8, -1.1)
 | Psychostimulant alone | 39.0 (7.68) | -11.3 (1.24) | ----------

a Difference (drug minus placebo) in least-squares mean change from baseline. SD: standard deviation; SE: standard error; LS Mean: least-squares mean; CI: unadjusted confidence interval.

Maintenance Monotherapy for ADHD

Study 3 was a double-blind, placebo-controlled, randomized-withdrawal study in pediatric patients 6 to 17 years (n=253) with DSM-IV-TR diagnosis of ADHD. The study consisted of a 10-week, open-label phase (4 weeks of dose optimization and 6 weeks of dose maintenance), a 26-week double-blind phase, and a 4-week taper-down and follow-up phase. All patients were initiated at 0.1 mg/day and increased at weekly intervals in increments of 0.1 mg/day until reaching personalized optimal dose (0.1, 0.2, 0.3 or 0.4 mg/day, as divided doses). Eligible patients had to demonstrate treatment response as defined by ≥ 30% reduction in ADHD-RS-IV total score and a Clinical Global Impression-Improvement score of 1 or 2 during the open label phase. Patients who sustained treatment response (n=135) until the end of the open label phase were randomly assigned to one of the two treatment groups, clonidine hydrochloride extended-release (N=68) and Placebo (N=67), to evaluate the long-term efficacy of maintenance dose of clonidine hydrochloride extended-release in the double-blind phase. The primary efficacy endpoint was the percentage of patients with treatment failure defined as a ≥ 30% increase (worsening) in ADHD-RS-IV total score and ≥ 2 points increase (worsening) in Clinical Global Impression – Severity Scale in 2 consecutive visits or early termination for any reason. A total of 73 patients experienced treatment failure in the double-blind phase: 31 patients (45.6%) in the clonidine hydrochloride extended-release group and 42 patients (62.7%) in the placebo group, with a statistically significant difference in the primary endpoint favoring clonidine (Table 7). The cumulative proportion of patients with treatment failure over time during the double-blind phase is displayed in Figure 2.

Table 7: Treatment Failure: Double-Blind Full Analysis Set (Study 3)

Study 3 | Double-Blind Full Analysis Set
Study 3 | Clonidine Hydrochloride Extended-Release Tablets | Placebo
Number of patients | 68 | 67
Number of treatment failures | 31 (45.6%) | 42 (62.7%)
Basis of Treatment Failure
Clinical criteriaa,b | 11 (16.2%) | 9 (13.4%)
Lack of efficacyc | 1 (1.5%) | 3 (4.5%)
Withdrawal of informed assent/consent | 4 (5.9%) | 20 (29.9%)
Other early terminations | 15 (22.1%) | 10 (14.9%)

ADHD-RS-IV = Attention Deficit Hyperactivity Disorder-Rating Scale-4th edition; CGI-S = Clinical Global Impression-Severity

a At the same 2 consecutive visits a (1) 30% or greater reduction in ADHD-RS-IV, and (2) 2-point or more increase in CGI-S.

bTwo patients (1 placebo and 1 clonidine hydrochloride extended-release tablets) withdrew consent, but met the clinical criteria for treatment failure.

cThree patients (all placebo) discontinued the study due to treatment failure, but met only the criterion for ADHD-RS-IV.

Figure 2: Kaplan-Meier Estimation of Cumulative Proportion of Pediatric Patients (6 to 17 Years) with Treatment Failure (Study 3)

Figure 2

16 HOW SUPPLIED/STORAGE AND HANDLING

How Supplied

ONYDA XR (clonidine hydrochloride) extended-release oral suspension 0.1 mg/mL is a light beige to tan viscous suspension.

ONYDA XR is supplied in a carton. Each carton contains one bottle with a child resistant closure, an oral dosing dispenser(s), and a press in bottle adapter(s).

Bottle of 30 mL | NDC 24478-148-03 | One (1) oral dosing dispenser and one (1) press in bottle adapter
Bottle of 60 mL | NDC 24478-148-04 | One (1) oral dosing dispenser and one (1) press in bottle adapter
Bottle of 120 mL | NDC 24478-148-02 | Two (2) oral dosing dispensers and two (2) press in bottle adapters

Storage and Handling

Store at 20°C to 25°C (68°F to 77°F); excursions permitted to 15°C to 30°C (59°F to 86°F) [see USP Controlled Room Temperature]. Protect from light.

Store and dispense ONYDA XR in the original bottle. Dispense with bottle adapter and oral dosing dispenser supplied in the carton.

For the bottles of 30 mL and 60 mL, discard any unused ONYDA XR 30 days after first opening the bottle.

For the 120 mL bottle, discard any unused ONYDA XR 60 days after first opening the bottle.

17 PATIENT COUNSELING INFORMATION

Advise the patient to read the FDA-approved patient labeling (Patient Information and Instructions for Use).

Dosage and Administration

Advise patients that ONYDA XR may be taken with or without food. When initiating treatment, provide titration instructions [see Dosage and Administration (2.1)].

Administration Instructions

Instruct patients to read the “Instructions for Use” for complete administration instructions [see Dosage and Administration (2.2)].

Advise patients to:

- firmly insert the bottle adapter into the bottle and do not remove the bottle adapter once inserted. Use the oral dispenser provided with ONYDA XR.
- gently shake ONYDA XR with a smooth up and down motion (to avoid foaming) for at least 10 seconds before each administration.
- For the bottles of 30 mL and 60 mL, discard any unused ONYDA XR 30 days after first opening the bottle.
- For the 120 mL bottle, discard any unused ONYDA XR 60 days after first opening the bottle.

Missed Dose

If patients miss a dose of ONYDA XR, advise them to skip the dose and take the next dose as scheduled and not to take more than the prescribed total daily amount of ONYDA XR in any 24‑hour period [see Dosage and Administration (2.5)].

Hypotension/Bradycardia

Advise patients who have a history of syncope or may have a condition that predisposes them to syncope, such as hypotension, orthostatic hypotension, bradycardia, or dehydration, to avoid becoming dehydrated or overheated [see Warnings and Precautions (5.1)].

Sedation and Somnolence

Instruct patients to use caution when driving a car or operating heavy equipment until they know how they will respond to treatment with ONYDA XR. Also advise patients to avoid the use of ONYDA XR with other centrally active depressants and with alcohol [see Warnings and Precautions (5.2)].

Rebound Hypertension

Advise patients not to discontinue ONYDA XR abruptly. Inform patients and caregivers that pediatric patients with gastrointestinal illnesses that lead to vomiting may be at increased risk for rebound hypertension [see Warnings and Precautions (5.3)].

Allergic Reactions

Advise patients to discontinue ONYDA XR and seek immediate medical attention if any signs or symptoms of a hypersensitivity reaction occur, such as generalized rash, urticaria, or angioedema [see Warnings and Precautions (5.4)].

Pregnancy Registry

Advise patients that there is a pregnancy exposure registry that monitors pregnancy outcomes in patients exposed to ONYDA XR during pregnancy [see Use in Specific Populations (8.1)].

Lactation

Advise breastfeeding women using ONYDA XR to monitor infants for excess sedation, decreased muscle tone, and respiratory depression and to seek medical care if they notice these signs [see Use in Specific Populations (8.2)].

Fertility

Advise females and males of reproductive potential that ONYDA XR may impair fertility [see Use in Specific Populations (8.3) and Nonclinical Toxicology (13.1)].

Manufactured by/Distributed by:

Tris Pharma, Inc.

Monmouth Junction, NJ 08852

www.trispharma.com

LB8735

Rev. 05

PATIENT INFORMATION

ONYDATM XR (oh-nee-dah)

(clonidine hydrochloride)

extended-release oral suspension

What is ONYDA XR?

ONYDA XR is a prescription medicine used for the treatment of Attention Deficit Hyperactivity Disorder (ADHD) alone or with certain other ADHD medicines in children 6 years of age and older.

It is not known if ONYDA XR is safe and effective in children under 6 years of age.

Who should not take ONYDA XR?

Do not take ONYDA XR if you are allergic to clonidine. See the end of this Patient Information for a complete list of ingredients in ONYDA XR.

Before taking ONYDA XR, tell your healthcare provider about all of your medical conditions, including if you:

- have kidney problems
- have low or high blood pressure
- have a history of passing out (syncope)
- have heart problems, including slow heart rate or other heart rhythm problems
- had a stroke or have stroke symptoms
- had an allergic reaction after taking clonidine through your skin in a transdermal system (patch)

- are pregnant or plan to become pregnant. It is not known if ONYDA XR will harm the unborn baby. Talk to your healthcare provider if you are pregnant or plan to become pregnant.
  - There is a pregnancy registry for females who are exposed to ADHD medications, including ONYDA XR, during pregnancy. The purpose of the registry is to collect information about the health of females exposed to ONYDA XR and their baby. If you become pregnant during treatment with ONYDA XR, talk to your healthcare provider about registering with the National Pregnancy Registry of ADHD Medications at 1-866-961-2388 or visit online at https://womensmentalhealth.org/adhdmedications/
- are breastfeeding or plan to breastfeed. ONYDA XR passes into the breast milk. Babies who are breastfed during treatment with ONYDA XR may become very sleepy, develop relaxed or floppy muscles, and develop trouble breathing. Call the baby’s healthcare provider if the baby is breastfed during treatment with ONYDA XR and develops any of these symptoms. Talk to your healthcare provider about the best way to feed your baby if you take ONYDA XR.

Tell your healthcare provider about all of the medicines that you take, including prescription and over-the-counter medicines, vitamins, and herbal supplements.

ONYDA XR and certain other medicines may affect each other causing serious side effects. Especially tell your healthcare provider if you take:

• anti-depression medicines • other medicines for ADHD
• heart or blood pressure medicines • medicines that cause sleepiness (sedation)
• other medicines that contain clonidine

Ask your healthcare provider or pharmacist if you are not sure if your medicine is listed above.

Know the medicines that you take. Keep a list of your medicines with you to show your healthcare provider and pharmacist when you get a new medicine.

How should I take ONYDA XR?

- Take ONYDA XR 1 time daily at bedtime with or without food.

- Take ONYDA XR exactly as your healthcare provider tells you.

- Your healthcare provider may change your dose of ONYDA XR. Do not change your dose of ONYDA XR without talking to your healthcare provider.

- If you are taking another clonidine medicine, stop taking it before you start treatment with ONYDA XR.
- The dose of ONYDA XR is not the same as other clonidine medicines. Do not change between ONYDA XR and other clonidine medicines unless your healthcare provider tells you.
- Do not stop taking ONYDA XR without talking to your healthcare provider.
- If you miss a dose of ONYDA XR, skip the missed dose and take the next dose at their regular scheduled time. Do not take more ONYDA XR in a 24-hour period than your healthcare provider prescribed for your daily dose.
- For the bottles of 30 mL and 60 mL, throw away (discard of) any remaining ONYDA XR if you have not used it 30 days after first opening the bottle.
- For the 120 mL bottle, throw away (discard of) any remaining ONYDA XR if you have not used it 60 days after first opening the bottle.
- See the detailed Instructions for Use for information on how to take a dose of ONYDA XR.

If you take too much ONYDA XR, call your healthcare provider or Poison Help line at 1-800-222-1222, or go to the nearest hospital emergency room right away.

What should I avoid while taking ONYDA XR?

- Do not become dehydrated or too hot (overheated) to decrease your chance of passing out during treatment with ONYDA XR.
- Do not drive, operate heavy machinery, or do other dangerous activities until you know how ONYDA XR affects you because ONYDA XR can cause sleepiness and tiredness that could cause slow reaction times.
- Do not drink alcohol or take other medicines that make you sleepy or dizzy during treatment with ONYDA XR until you talk with your healthcare provider. Taking ONYDA XR with alcohol or medicines that cause sleepiness or dizziness may make your sleepiness or dizziness worse.
- Do not suddenly stop ONYDA XR. Tell your healthcare provider if you have been vomiting and cannot take ONYDA XR, you may be at risk for rebound hypertension.

What are possible side effects of ONYDA XR?

ONYDA XR may cause serious side effects, including:

- Decreased blood pressure and heart rate. ONYDA XR can decrease your blood pressure and heart rate, which can increase your chance of passing out (syncope). If you have a history of passing out or have other medical problems or take other medicines that increase your risk of passing out, your risk is higher. Your healthcare provider should check your heart rate and blood pressure before starting treatment and regularly during treatment with ONYDA XR. See “What should I avoid while taking ONYDA XR?”
- Sleepiness and tiredness that could cause slow reaction times (sedation and somnolence). See “What should I avoid while taking ONYDA XR?”
- Rebound high blood pressure (hypertension). Suddenly stopping ONYDA XR can cause high blood pressure to return if you have a history of high blood pressure. Suddenly stopping ONYDA XR may also cause withdrawal symptoms including headache, increased heart rate, nausea, flushing or warm feeling, lightheadedness, tightness in your chest and nervousness or anxiety. Do not suddenly stop ONYDA XR treatment without first talking to your healthcare provider.

- Allergic reactions. You may develop an allergic reaction to ONYDA XR if you had an allergic reaction to clonidine taken through your skin in a patch. Stop taking ONYDA XR and call your healthcare provider right away or go to the nearest emergency room if you develop any signs or symptoms of an allergic reaction, including:

o skin rash o hives o swelling of the eyes, face, lips, or tongue

The most common side effects of ONYDA XR when used alone include:

• falling asleep or sleepiness and tiredness that could cause slow reaction times • nightmare • constipation
• irritability • trouble sleeping • dry mouth

The most common side effects of ONYDA XR when used with other ADHD medicines include:

• falling asleep or sleepiness and tiredness that could cause slow reaction times • decreased appetite • dizziness

ONYDA XR may cause fertility problems in females and males, which may affect your ability to have a child. Talk to your healthcare provider if this is a concern for you.

These are not all of the possible side effects of ONYDA XR.

Call your doctor for medical advice about side effects. You may report side effects to FDA at 1-800-FDA-1088.

How should I store ONYDA XR?

- Store ONYDA XR at room temperature between 68°F to 77°F (20°C to 25°C).
- Protect from light and keep ONYDA XR in the original container. Tightly close the child-resistant cap.
- For the bottles of 30 mL and 60 mL, throw away (discard of) any remaining ONYDA XR if you have not used it 30 days after first opening the bottle.
- For the 120 mL bottle, throw away (discard of) any remaining ONYDA XR if you have not used it 60 days after first opening the bottle.

Keep ONYDA XR and all medicines out of the reach of children.

General information about the safe and effective use of ONYDA XR.

Medicines are sometimes prescribed for purposes other than those listed in a Patient Information leaflet. Do not use ONYDA XR for a condition for which it was not prescribed. Do not give ONYDA XR to other people, even if they have the same symptoms that you have. It may harm them. You can also ask your pharmacist or healthcare provider for information about ONYDA XR that is written for health professionals.

What are the ingredients in ONYDA XR?

Active Ingredient: clonidine hydrochloride

Inactive Ingredients: anhydrous citric acid, edetate disodium, glycerin, modified starch, methylparaben, orange flavor, polyvinyl acetate dispersion 30%, povidone, polysorbate 80, propylparaben, purified water, sucrose, sodium polystyrene sulfonate, triacetin, and xanthan gum

Manufactured by/Distributed by:

Tris Pharma, Inc.

Monmouth Junction, NJ 08852

www.trispharma.com

For more information about ONYDA XR call 1-732-940-0358.

Rev. 04

This Patient Information has been approved by the U.S. Food and Drug Administration. Revised:04/2025

INSTRUCTIONS FOR USE

ONYDATM XR (oh-nee-dah)

(clonidine hydrochloride)

extended-release oral suspension

This Instructions for Use contains information on how to take ONYDA XR.

Important Information You Need to Know Before Taking ONYDA XR:

- ONYDA XR is for oral use only (taken by mouth).
- Take ONYDA XR with or without food.
- Use only the oral dosing syringe and bottle adapter that come with ONYDA XR to measure and take a dose of ONYDA XR.
- Shake the ONYDA XR bottle gently.
- Check the expiration date (EXP) on the carton label. Do not take ONYDA XR after the expiration date has passed. Call your healthcare provider or pharmacist if your medicine is expired.
- For the bottles of 30 mL and 60 mL, throw away (discard of) any remaining ONYDA XR if you have not used it 30 days after first opening the bottle.
- For the 120 mL bottle, throw away (discard of) any remaining ONYDA XR if you have not used it 60 days after first opening the bottle.

Supplies included in the ONYDA XR carton:

1 bottle of ONYDA XR | Dosing Syringe(s) | Bottle Adapter(s)
30 mL bottle | 1 | 1
60 mL bottle | 1 | 1
120 mL bottle | 2 | 2

Figure A

Figure A

Step 1:

Preparing to take ONYDA XR:

- Wash and dry your hands (see Figure B).
- Remove the ONYDA XR bottle, 1 oral dosing syringe, and 1 bottle adapter from the carton.

Tell your pharmacist right away if you are missing any supplies from the carton.

Figure B

Step 2:

- Place the ONYDA XR bottle on a flat surface like a table or countertop and remove the child resistant cap by pressing down and turning counterclockwise (see Figure C).
  Insert the bottle adapter (first time use only).
- Hold the bottle firmly and insert the ridged end of the bottle adapter into the neck of the bottle.
- Firmly push the bottle adapter all the way down with your thumb until the top of the adapter is aligned and flat (flush) with the top of the bottle (See Figure D).
- Do not remove the bottle adapter once it has been inserted into the bottle.

Figure C
Figure D

Step 3:

- Put the cap back on the bottle and close it tightly by turning the cap clockwise (see Figure E).
- Shake the bottle gently with a smooth up and down motion to avoid foaming (see Figure F).
- Shake the bottle gently for at least 10 seconds before you take each dose.

Figure E
Figure F

Step 4:

Place the ONYDA XR bottle upright on the table or countertop. Open the cap again by pressing down and turn counterclockwise to remove the cap (see Figure G).

Figure G

Step 5:

- Check the ONYDA XR oral dosing syringe to find the right dose in milliliters (mL) that has been prescribed by the healthcare provider (see Figure H).
- Make sure the oral dosing syringe is dry.

Figure H

Step 6:

- Insert the tip of the oral dosing syringe through the adapter into the bottle (see Figure I).
- Push the plunger all the way down (see Figure J).

Figure I
Figure J

Step 7:

Measuring the dose of ONYDA XR:

- With the tip of the oral dosing syringe in place in the adapter, hold the ONYDA XR bottle with 1 hand and turn the bottle upside down. Pull the plunger down until the white end of the plunger reaches the number of mL you need for the prescribed dose (see Figure K).
- Push and pull the plunger a few times to make sure that there are no air bubbles.
- Tap the barrel of the oral dosing syringe if needed to get rid of any air bubbles (see Figure L).

Figure K
Figure L

Step 8:

- Turn the bottle over and place it upright on a table or countertop, then remove the oral dosing syringe from the bottle adapter (see Figure M).

Figure M

Step 9:

- Check that the correct dose in mL was pulled up into the oral dosing syringe (see Figure N).
- If the dose is not correct:

- Insert the oral syringe tip back into the bottle and fully push in the plunger to the bottom of the syringe barrel so that all of the oral suspension flows back into the bottle.
- Repeat Steps 6 through 8.

Figure N

Step 10:

Taking the dose of ONYDA XR:

- The child should be in a seated position before taking ONYDA XR.
- Tilt the head slightly upwards.
- Place the oral dosing syringe into the mouth and point it toward the cheek (see Figure O).
  - Close the mouth tightly around the oral dosing syringe and slowly push the plunger all the way down to give the ONYDA XR dose (see Figure P).
- After all the medication has been taken, remove the oral dosing syringe from the mouth.

Figure O
Figure P

Step 11:

Closing the bottle:

- Put the ONYDA XR cap back on the bottle and close the cap tightly by turning the cap clockwise (see Figure Q).

Figure Q

Step 12:

Cleaning up:

- Clean the oral dosing syringe after each use by rinsing with tap water (see Figure R).
- Allow the oral dosing syringe to dry and keep it in a safe place for the next use.
- Wash and dry your hands.

Figure R

Disposing of ONYDA XR:

- Throw away any unused or expired ONYDA XR in your household trash.
- For the bottles of 30 mL and 60 mL, throw away (discard of) any remaining ONYDA XR if you have not used it 30 days after first opening the bottle.
- For the 120 mL bottle, throw away (discard of) any remaining ONYDA XR if you have not used it 60 days after first opening the bottle.

Storing ONYDA XR:

- Store ONYDA XR at room temperature between 68°F to 77°F (20°C to 25°C).
- Protect from light and keep ONYDA XR in the original container. Tightly close the child-resistant cap.

Keep ONYDA XR and all medicines out of the reach of children.

Manufactured by/Distributed by:

Tris Pharma, Inc.

Monmouth Junction, NJ 08852

LB8730 Rev. 03

This Instructions for Use has been approved by the U.S. Food and Drug Administration

Revised: 02/2025

PRINCIPAL DISPLAY PANEL

NDC 24478-148-01
ONYDATM XR

(clonidine hydrochloride) extended-release oral suspension

0.1 mg
Shake Gently Before Use

7 mL Rx only

PRINCIPAL DISPLAY PANEL

NDC 24478-148-03
ONYDATM XR

(clonidine hydrochloride) extended-release oral suspension

0.1 mg
Shake Gently Before Use
30 mL Rx only